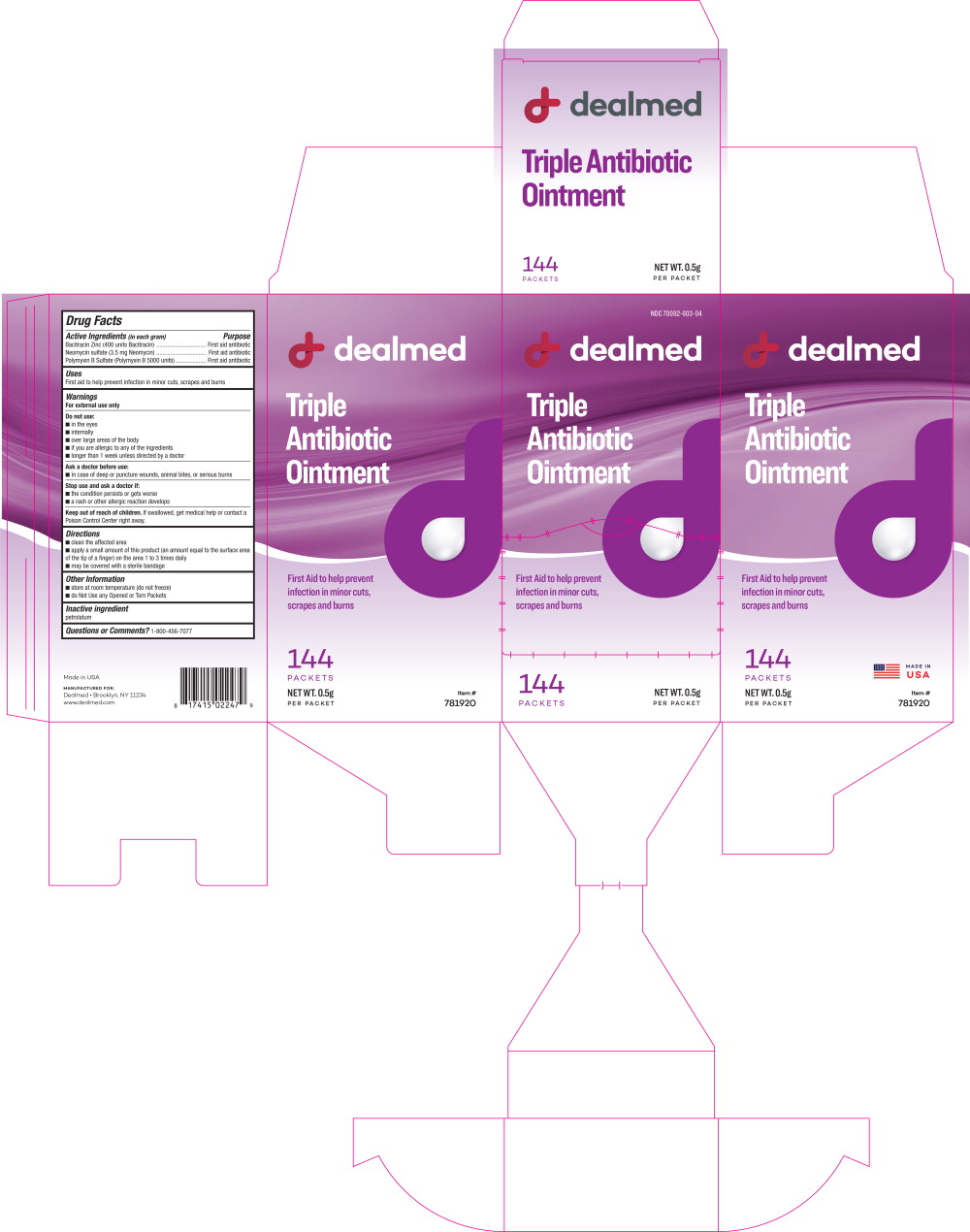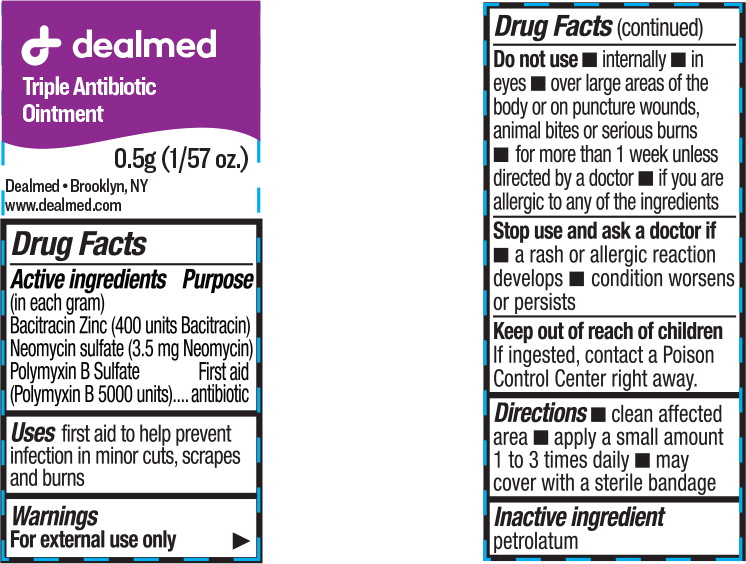 DRUG LABEL: Triple Antibiotic
NDC: 70082-603 | Form: OINTMENT
Manufacturer: Dealmed Medical Supplies LLC
Category: otc | Type: HUMAN OTC DRUG LABEL
Date: 20220308

ACTIVE INGREDIENTS: bacitracin zinc 400 [iU]/1 g; neomycin sulfate 3.5 mg/1 g; polymyxin b sulfate 5000 [iU]/1 g
INACTIVE INGREDIENTS: petrolatum

Drug Facts

Active Ingredients (in each gram)

Bacitracin Zinc (400 units Bacitracin)

Neomycin sulfate (3.5 mg Neomycin)

Polymyxin B Sulfate (Polymyxin B 5000 units)

Purpose

First aid antibiotic

First aid antibiotic

First aid antibiotic

Uses

First aid to help prevent infection in minor cuts, scrapes and burns

Warnings

For external use only

Do not use:

- in the eyes
- internally
- over large areas of the body
- if you are allergic to any of the ingredients
- longer than 1 week unless directed by a doctor

Ask a doctor before use:

- in case of deep or puncture wounds, animal bites, or serious burns

Stop use and ask a doctor if:

- the condition persists or gets worse
- a rash or other allergic reaction develops

Keep out of reach of children. If swallowed, get medical help or contact a Poison Control Center right away.

Directions

- clean the affected area
- apply a small amount of this product (an amount equal to the surface area of the tip of a finger) on the area 1 to 3 times daily
- may be covered with a sterile bandage

Other Information

- store at room temperature (do not freeze)
- do Not Use any Opened or Torn Packets

Inactive ingredient

petrolatum

Questions or Comments?

1 -800-456-7077

Principal Display Panel - 0.5 g Box Label

NDC 70082-603-04

dealmed

Triple
Antibiotic
Ointment

First Aid to help prevent
infection in minor cuts,
scrapes and burns

144
PACKETS

NET WT. 0.5g
PER PACKET

Principal Display Panel - 0.5g Pouch Label

dealmed

Triple Antibiotic
Ointment

0.5g (1/57 oz.)

Dealmed • Brooklyn, NY

www.dealmed.com